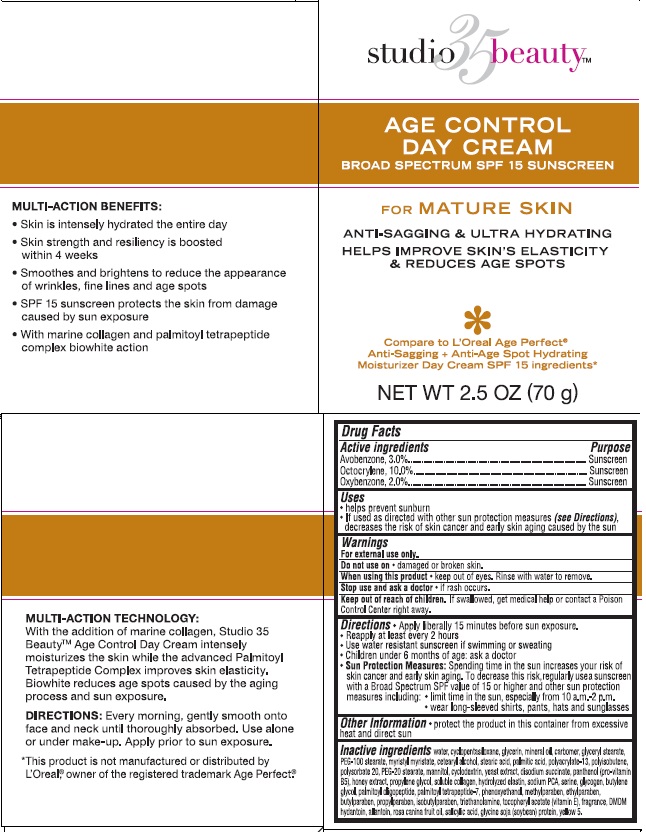 DRUG LABEL: Walgreens Anti-Sagging and Ultra Hydrating Day Broad Spectrum SPF15 Sunscreen
NDC: 0363-9688 | Form: CREAM
Manufacturer: Walgreen Company
Category: otc | Type: HUMAN OTC DRUG LABEL
Date: 20140903

ACTIVE INGREDIENTS: AVOBENZONE 3 g/100 g; OXYBENZONE 2 g/100 g; OCTOCRYLENE 10 g/100 g
INACTIVE INGREDIENTS: WATER; CYCLOMETHICONE 5; GLYCERIN; MINERAL OIL; CARBOMER COPOLYMER TYPE A (ALLYL PENTAERYTHRITOL CROSSLINKED); GLYCERYL 1-STEARATE; PEG-100 STEARATE; MYRISTYL MYRISTATE; CETOSTEARYL ALCOHOL; STEARIC ACID; PALMITIC ACID; SODIUM POLYACRYLATE (2500000 MW); POLYISOBUTYLENE (1000 MW); POLYSORBATE 20; PEG-20 STEARATE; MANNITOL; YEAST; SODIUM SUCCINATE ANHYDROUS; PANTHENOL; HYDROLYZED ELASTIN, BOVINE, ALKALINE (1000 MW); BUTYLENE GLYCOL; PALMITOYL OLIGOPEPTIDE; PALMITOYL TETRAPEPTIDE-7; PHENOXYETHANOL; METHYLPARABEN; ETHYLPARABEN; BUTYLPARABEN; PROPYLPARABEN; ISOBUTYLPARABEN; TROLAMINE; .ALPHA.-TOCOPHEROL ACETATE; DMDM HYDANTOIN; ALLANTOIN; ROSA CANINA FRUIT OIL; SALICYLIC ACID; SOY STEROL; FD&C YELLOW NO. 5; HONEY; PROPYLENE GLYCOL; BOVINE TYPE I COLLAGEN; SODIUM PYRROLIDONE CARBOXYLATE; SERINE; GLYCOGEN

studio 35 beauty™ Age Control Day Cream

Active ingredient

Avobenzone 3.0%
Octocrylene 10.0%
Oxybenzone 2.0%

Purpose

Sunscreen

Uses

- helps prevent sunburn
- If used as directed with other sun protection measures (see Directions), decreases the risk of skin cancer and early skin aging caused by the sun

Warnings

For external use only.

Do not use on

- damaged or broken skin

When using this product

- keep out of eyes. Rinse with water to remove.

Stop use and ask a doctor

- if rash occurs.

Keep Out of Reach of Children.

If swallowed, get medical help or contact a Poison Control Center right away.

Directions

- Apply liberally 15 minutes before sun exposure.
- Reapply at least every 2 hours
- Use water resistant sunscreen if swimming or sweating
- Children under 6 months of age: ask a doctor
- Sun Protection Measures: Spending time in the sun increases your risk of skin cancer and early skin aging. To decrease this risk, regularly use a sunscreen with a Broad Spectrum SPF value of 15 or higher and other sun protection measures including:
  1. limit time in the sun, especially from 10 a.m. - 2 p.m.
  2. wear long-sleeved shirts, pants, hats and sunglasses

Other Information

1. protect the product in this container from excessive heat and direct sun

Inactive ingredients

water, cyclopentasiloxane, glycerin, mineral oil, carbomer, glyceryl stearate, PEG-100 stearate, myristyl myristate, cetearyl alcohol, stearic acid, palmitic acid, polyacrylate-13, polyisobutene, polysorbate 20, PEG-20 stearate, mannitol, cyclodextrin, yeast extract, disodium succinate, panthenol (pro-vitamin B5), honey extract, propylene gycol, soluble collagen, hydrolyzed elastin, sodium PCA, serine, glycogen, butylene glycol, palmitoyl oligopeptide, palmitoyl tetrapeptide-7, phenoxyethanol, methylparaben, ethylparaben, butylparaben, propylparaben, isobutylparaben, triethanolamine, tocopheryl acetate (vitamin E), fragrance, DMDM hydantoin, allantoin, rosa canina fruit oil, salicylic acid, glycine soja (soybean) protein, yellow 5.

Package/Label Principal Display Panel

studio 35 beauty™ Age Control Day Cream Broad Spectrum SPF 15 Sunscreen

For Mature Skin
Anti-Sagging & Ultra Hydrating
Helps Improve Skin's Elasticity & Reduces Age Spots

Compare to L'Oreal Age Perfect® Anti-Sagging + Anti-Age Spot Hydrating Moisturizer Day Cream SPF 15 ingredients

Net Wt 2.5 Oz (70 g)

Jar Label